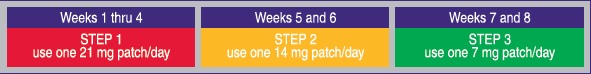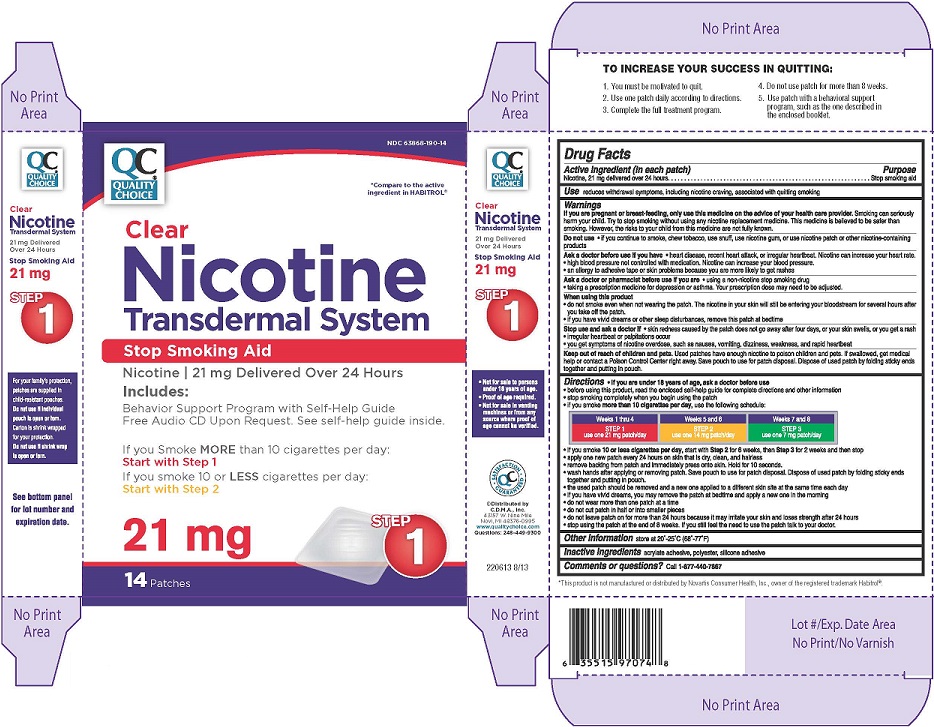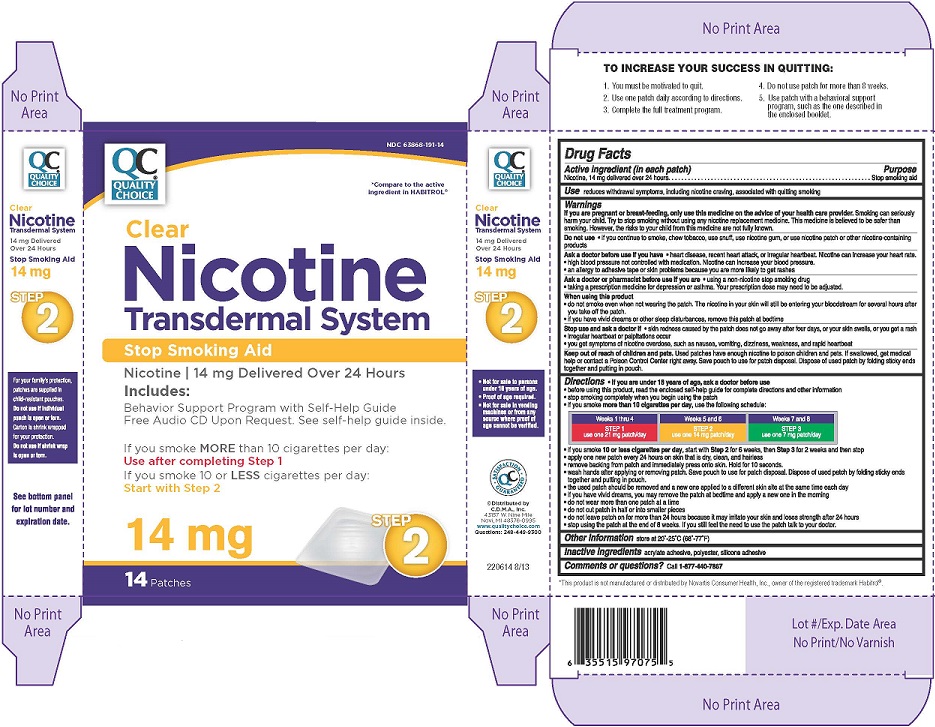 DRUG LABEL: Nicotine Transdermal System
NDC: 63868-190 | Form: PATCH, EXTENDED RELEASE
Manufacturer: Chain Drug Marketing Association Inc.
Category: otc | Type: HUMAN OTC DRUG LABEL
Date: 20140619

ACTIVE INGREDIENTS: NICOTINE 21 mg/24 h
INACTIVE INGREDIENTS: HEPTANE; XYLENE; ETHYL ACETATE; ISOPROPYL ALCOHOL; TOLUENE; ETHYLBENZENE; VINYL ACETATE; HIGH DENSITY POLYETHYLENE

Nicotine Transdermal System, Step 1 and Step 2

Drug Facts

Active ingredient (in each patch)

Active ingredient Step 1
Nicotine, 21mg delivered over 24 hours

Active ingredient Step 2
Nicotine, 14 mg delivered over 24 hours

Purpose

Stop smoking aid

Use

reduces withdrawal symptoms, including nicotine craving, associated with quitting smoking

Warnings

If you are pregnant or breast-feeding, only use this medicine on the advice of your health care provider. Smoking can seriously harm your child. Try to stop smoking without using any nicotine replacement medicine. This medicine is believed to be safer than smoking. However, the risks to your child from this medicine are not fully known.

Do not use

- if you continue to smoke, chew tobacco, use snuff, use nicotine gum, or use nicotine patch or other nicotine-containing products

Ask a doctor before use if you have

- heart disease, recent heart attack, or irregular heartbeat. Nicotine can increase your heart rate.
- high blood pressure not controlled with medication. Nicotine can increase your blood pressure.
- an allergy to adhesive tape or skin problems because you are more likely to get rashes

Ask a doctor or a pharmacist before use if you are

- using a non-nicotine stop smoking drug
- taking a prescription medicine for depression or asthma. Your prescription dose may need to be adjusted.

When using this product

- do not smoke even when not wearing the patch. The nicotine in your skin will still be entering your bloodstream for several hours after you take off the patch.
- if you have vivid dreams or other sleep disturbances remove this patch at bedtime

Stop use and ask a doctor if

- skin redness caused by the patch does not go away after four days, or your skin swells, or you get a rash
- irregular heartbeat or palpitations occur
- you get symptoms of nicotine overdose, such as nausea, vomiting, dizziness, weakness and rapid heartbeat

Keep out of reach of children and pets.

Used patches have enough nicotine to poison children and pets. If swallowed, get medical help or contact a Poison Control Center right away. Save pouch to use for patch disposal. Dispose of used patch by folding sticky ends together and putting in pouch.

Directions

- if you are under 18 years of age, ask a doctor before use
- before using this product, read the enclosed self-help guide for complete directions and other information
- stop smoking completely when you begin using the patch
- if you smoke more than 10 cigarettes per day, use the following schedule:

- if you smoke 10 or less cigarettes per day, start with Step 2 for 6 weeks, then Step 3 for 2 weeks and then stop
- apply one new patch every 24 hours on skin that is dry, clean and hairless
- remove backing from patch and immediately press onto skin. Hold for 10 seconds.
- wash hands after applying or removing patch. Save pouch to use for patch disposal. Dispose of used patch by folding sticky ends together and putting in pouch.
- the used patch should be removed and a new one applied to a different skin site at the same time each day
- if you have vivid dreams, you may remove the patch at bedtime and apply a new one in the morning
- do not wear more than one patch at a time
- do not cut patch in half or into smaller pieces
- do not leave patch on for more than 24 hours because it may irritate your skin and loses strength after 24 hours
- stop using the patch at the end of 8 weeks. If you still feel the need to use the patch talk to your doctor.

Other information

store at 20°-25°C (68°-77°F)

Inactive ingredients

acrylate adhesive, polyester, silicone adhesive

Comments or questions?

Call 1-877-440-7867

Principal Display Panel

NDC 63868-190-14

*Compare to the active ingredient in HABITROL®

Clear
Nicotine
Transdermal System
Step 1

Stop Smoking Aid
Nicotine/21 mg Delivered Over 24 Hours
Includes:
Behavior Support Program with Self-Help Guide
Free Audio CD Upon Request. See self-help guide inside.

If you Smoke MORE than 10 cigarrettes per day:
Start with Step 1
If you smoke 10 or LESS cigarrettes per day:
Start with Step 2

21 mg
14 Pactches

©Distributed by
C.D.M.A, Inc.
Novi, MI 48376-0995
www.qualitychoice.com
Questions: 248-449-9300

Principal Display Panel

NDC 63868-190-14

*Compare to the active ingredient in HABITROL®

Clear
Nicotine
Transdermal System
Step 2

Stop Smoking Aid
Nicotine/21 mg Delivered Over 24 Hours
Includes:
Behavior Support Program with Self-Help Guide
Free Audio CD Upon Request. See self-help guide inside.

If you Smoke MORE than 10 cigarrettes per day:
Start with Step 1
If you smoke 10 or LESS cigarrettes per day:
Start with Step 2

14 mg
14 Pactches

©Distributed by
C.D.M.A, Inc.
Novi, MI 48376-0995
www.qualitychoice.com
Questions: 248-449-9300